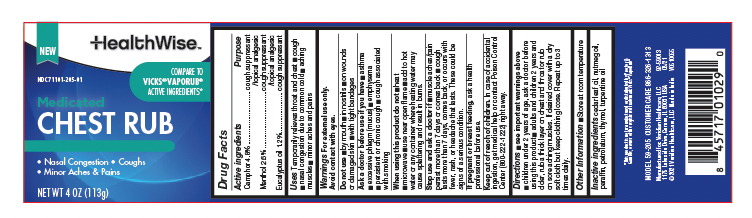 DRUG LABEL: HealthWise Chest Rub
NDC: 71101-205 | Form: OINTMENT
Manufacturer: Veridian Healthcare
Category: otc | Type: HUMAN OTC DRUG LABEL
Date: 20260118

ACTIVE INGREDIENTS: CAMPHOR (SYNTHETIC) 0.048 g/1 g; EUCALYPTUS OIL 0.012 g/1 g; MENTHOL 0.026 g/1 g
INACTIVE INGREDIENTS: PARAFFIN; CEDAR LEAF OIL; NUTMEG OIL; THYMOL; TURPENTINE OIL; PETROLATUM

HealthWise Chest Rub

Drug Facts

Active ingredients

Camphor 4.8%
Eucalyptus oil 1.2%
Menthol 2.6%

Purpose

Camphor 4.8% Cough suppressant, topical analgesic
Menthol 2.6% Cough suppressant, topical analgesic

Eucalyptus oil 1.2% Cough suppressant

Uses

- Temporarily relieves throat and chest
- cough
- nasal congestion due to common cold
- aching muscles
- minor aches and pains

Warnings

For external use only; avoid contact with eyes.

Do not use

- by mouth
- in nostrils
- on wounds or damaged skin
- with tight bandages

Ask a doctor before use if you have

- asthma
- excessive phlegm (mucus)
- emphysema
- persistent or chronic cough
- cough associated with smoking

When using this product, do not

- heat
- microwave
- use near open flame
- add to hot water or any container where heating water may cause splattering and result in burns

Stop use and ask a doctor if

- muscle aches/pain persist more than 7 days or comes back
- cough lasts more than 7 days or comes back, or occurs with fever, rash, or headache that lasts. These could be signs of a serious condition.

PREGNANCY OR BREAST FEEDING

If pregnant or breast-feeding, ask a health professional before use.

Keep out of reach of children. In case of accidental ingestion, get medical help or contact a Poison Control Center (800-222-1222) right away.

Directions

see important warnings under " When using this product"

- children under 2 years of age, ask a doctor before using this product

adults and children 2 years and over:

- rub a thick layer on chest & fractor rub on sore aching muscles. If desired cover with a dry soft cloth but keep clothing loose. Repeat up to 3 times daily

Other information

- store at room temperature

Inactive ingredients

cedar leaf oil, nutmeg oil, paraffin, petrolatum, thymol, turpentine oil